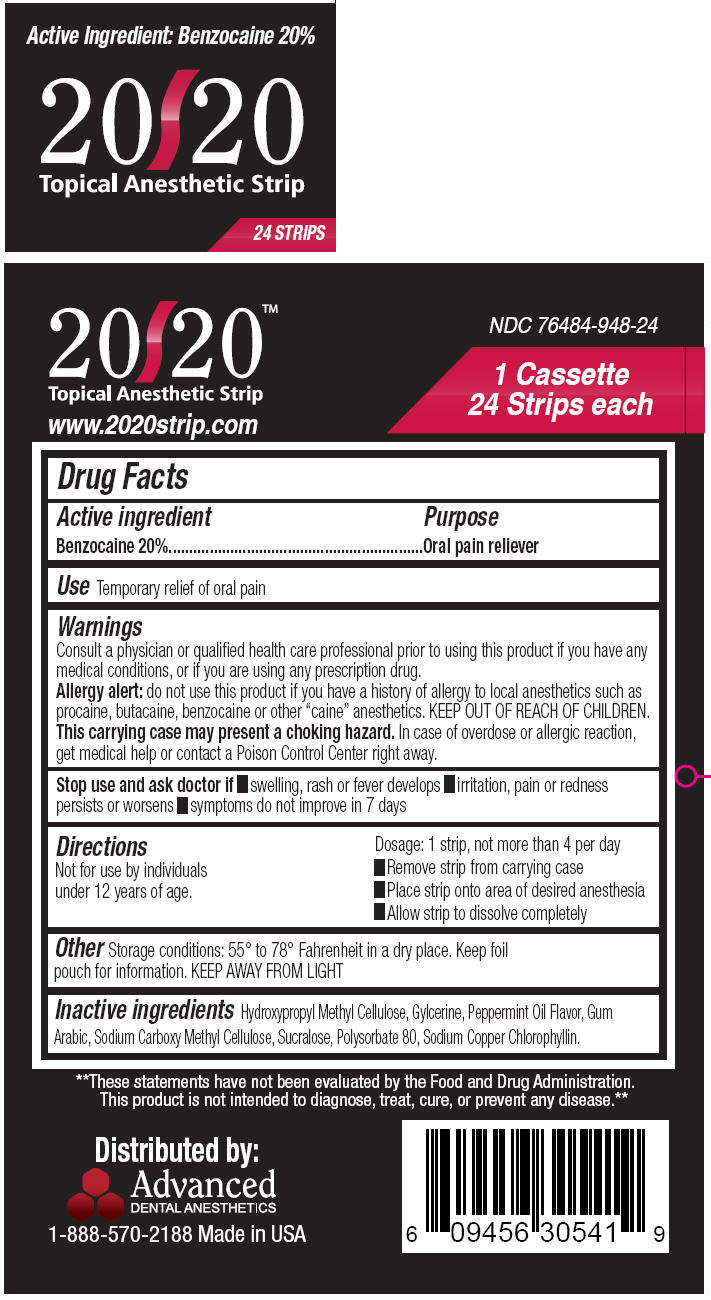 DRUG LABEL: 20/20  
NDC: 76484-948 | Form: STRIP
Manufacturer: Advanced Dental Anesthetics
Category: otc | Type: HUMAN OTC DRUG LABEL
Date: 20120508

ACTIVE INGREDIENTS: BENZOCAINE 10 mg/1 1
INACTIVE INGREDIENTS: HYPROMELLOSE 2208 (3 MPA.S) 18.44 mg/1 1; HYPROMELLOSE 2208 (100 MPA.S); HYPROMELLOSE 2208 (4000 MPA.S); GLYCERIN; PEPPERMINT OIL; ACACIA; CARBOXYMETHYLCELLULOSE SODIUM; SUCRALOSE; POLYSORBATE 80; SODIUM COPPER CHLOROPHYLLIN

20/20 Topical Anesthetic Strip

Drug Facts

Active ingredient

Benzocaine 20%

Purpose

Oral pain reliever

Use

Temporary relief of oral pain

Warnings

ASK DOCTOR/PHARMACIST

Consult a physician or qualified health care professional prior to using this product if you have any medical conditions, or if you are using any prescription drug.

Allergy alert

do not use this product if you have a history of allergy to local anesthetics such as procaine, butacaine, benzocaine or other "caine" anesthetics.

KEEP OUT OF REACH OF CHILDREN.

This carrying case may present a choking hazard. In case of overdose or allergic reaction, get medical help or contact a Poison Control Center right away.

Stop use and ask doctor if

- swelling, rash or fever develops
- irritation, pain or redness persists or worsens
- symptoms do not improve in 7 days

Directions

Not for use by individuals under 12 years of age.

Dosage: 1 strip, not more than 4 per day

- Remove 1 strip from carrying case.
- Place strip onto area of desired anesthesia
- Allow strip to dissolve completely

Other

Storage conditions: 55° to 78° Fahrenheit in a dry place. Keep foil pouch for information. KEEP AWAY FROM LIGHT

Inactive ingredients

Hydroxypropyl Methyl Cellulose, Gylcerine, Peppermint Oil Flavor, Gum Arabic, Sodium Carboxy Methyl Cellulose, Sucralose, Polysorbate 80, Sodium Copper Chlorophyllin.

Distributed by:
Advanced
DENTAL ANESTHETICS

PRINCIPAL DISPLAY PANEL - 24 Strip Pouch Label

Active Ingredient: Benzocaine 20%

20/20
Topical Anesthetic Strip

24 STRIPS